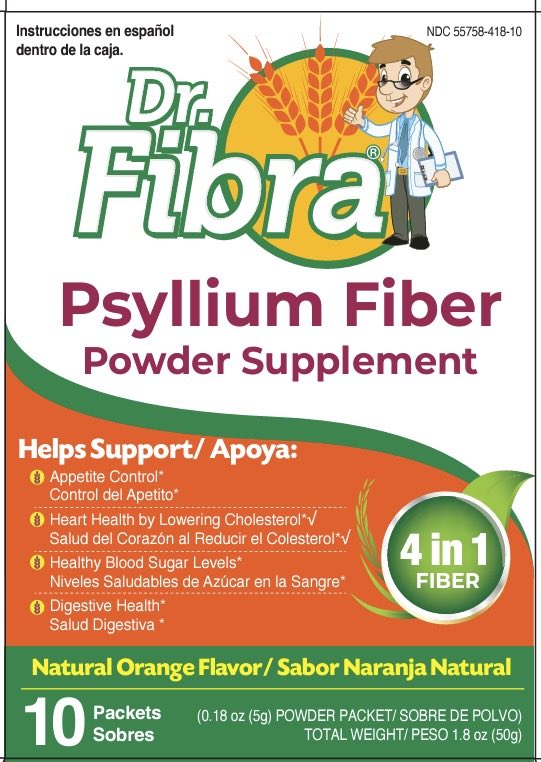 DRUG LABEL: Dr. Fibra
NDC: 55758-418 | Form: POWDER
Manufacturer: Pharmadel LLC
Category: otc | Type: HUMAN OTC DRUG LABEL
Date: 20240722

ACTIVE INGREDIENTS: PSYLLIUM HUSK 3.4 g/1 1
INACTIVE INGREDIENTS: ANHYDROUS CITRIC ACID; SODIUM BICARBONATE; FD&C YELLOW NO. 6; POVIDONE K30; SUCRALOSE

Dr. Fiber (V)

Active ingredient and Purpose

Active ingredient (in each packet) | Purpose
Psyllium seed husk 3.4 g.................... | Bulk-forming laxative

Uses

For relief of occasional constipation (irregularity). This product generally produces bowel movement in 12 to 72 hours.

Warnings

Choking: Taking this product without adequate fluid may cause it to swell and block your throat or esophagus and may cause choking. Do not take this product if you have difficulty in swallowing. If you experience chest pain, vomiting, or difficulty in swallowing or breathing after taking this product, seek immediate medical attention.

Allergy Alert: This product may cause allergic reactions in people, sensitive to inhaled or ingested psyllium.

Do not use

- if allergic to any ingredient in this product

Ask a doctor before use if you have

- abdominal pain, nausea or vomiting
- noticed a sudden change in bowel habits that persists over a period of 2 weeks
- a sodium restricted diet

Ask a doctor or pharmacist before use if you

are taking any other drug. Laxatives may affect how other drugs work.

When using this product

- take this product 2 hours before or after other drugs

Stop use and ask a doctor if

• constipation lasts more than 7 days
• rectal bleeding occurs
• you fail to have a bowel movement after use of a laxative. These may be signs of a serious condition.

If pregnant or breast-feeding,

ask a health professional before use.

Keep out of reach of children.

In case of overdose, get medical help or contact a Poison Control Center right away.

Directions

- mix this product (child or adult dose) with at least 8 ounces (a full glass) of water or other fluid. Taking this product without enough liquid may cause choking. See choking warning.

adults and children 12 years of age and older | 1 packet up to 3 times a day
children 6 to under 12 years of age | 1/2 packet up to 3 times a day
children under 6 years of age | consult a doctor

First time users: Start with the 1 packet per day, gradually increase to 3 times a day, as necessary. As your body adjust to increased fiber intake, you may experience changes in bowel habits and/or minor bloating.

Other information

- each packet contains: potassium 36 mg; sodium 178 mg
- store below 86°F (30°C)

Inactive ingredients

anhydrous citric acid, FD&C yellow #6, flavors, povidone k-30, sodium bicarbonate, sucralose

Questions?

+1-866-359-3478 (M-F) 9 AM - 5 PM EST or www.pharmadel.com

Dist. by:

Pharmadel LLC.

New Castle, DE 19720